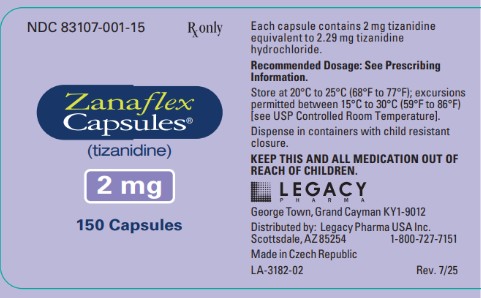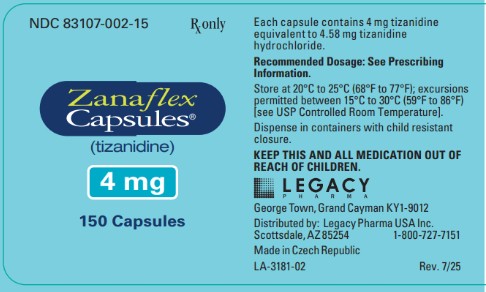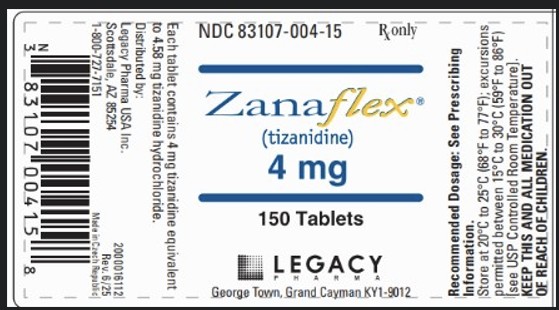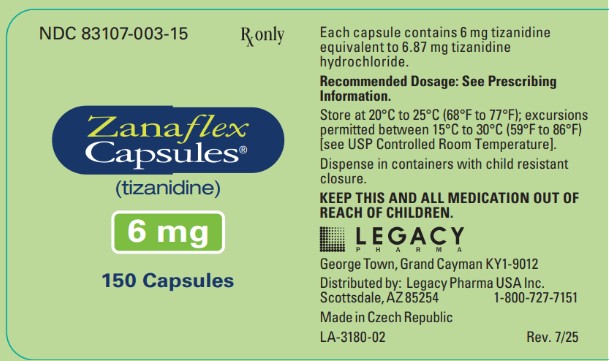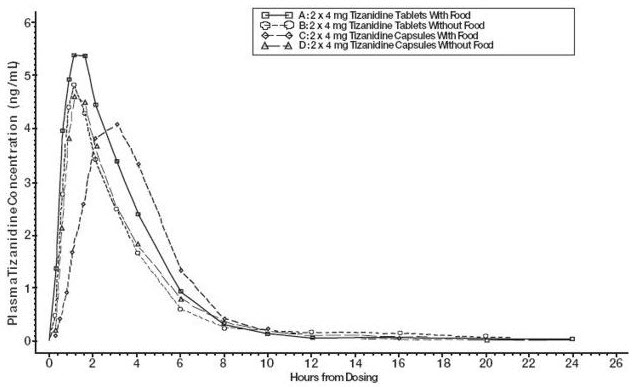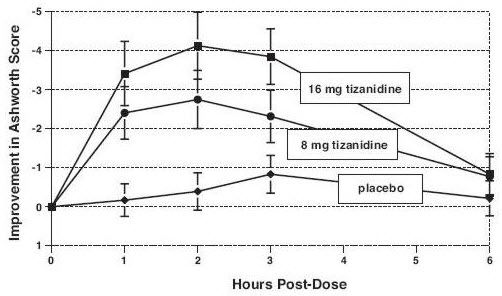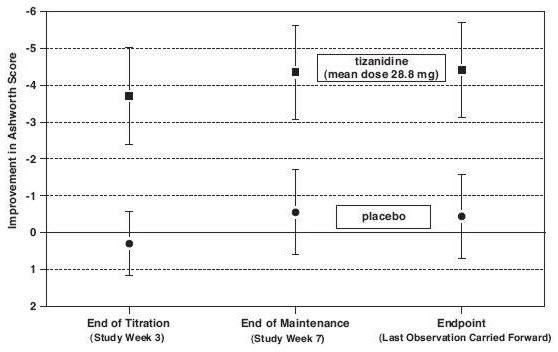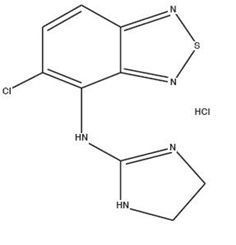 DRUG LABEL: Zanaflex
NDC: 83107-001 | Form: CAPSULE
Manufacturer: Legacy Pharma USA, Inc.
Category: prescription | Type: HUMAN PRESCRIPTION DRUG LABEL
Date: 20260102

ACTIVE INGREDIENTS: TIZANIDINE HYDROCHLORIDE 2 mg/1 1
INACTIVE INGREDIENTS: SILICON DIOXIDE; TITANIUM DIOXIDE; GELATIN, UNSPECIFIED; HYPROMELLOSE, UNSPECIFIED

HIGHLIGHTS OF PRESCRIBING INFORMATION

These highlights do not include all the information needed to use ZANAFLEX®safely and effectively. See full prescribing information for ZANAFLEX.
ZANAFLEX®(tizanidine) capsules, for oral use
ZANAFLEX®(tizanidine) tablets, for oral use
Initial U.S. Approval: 1996

RECENT MAJOR CHANGES

Indications and Usage (1) 11/2024

Dosage and Administration (2.1, 2.2, 2.3, 2.4, 2.5, 2.6) 11/2024

Contraindications (4) 11/2024

Warnings and Precautions (5.1, 5.2, 5.4, 5.5) 11/2024

1 INDICATIONS AND USAGE

Zanaflex is a central alpha-2-adrenergic agonist indicated for the treatment of spasticity. (1)

2 DOSAGE AND ADMINISTRATION

- Monitoring of aminotransferase levels is recommended at baseline and 1 month after maximum dose is achieved. (2.1)
- Recommended starting dose: 2 mg by mouth every 6 to 8 hours, as needed, up to a maximum of 3 doses in 24 hours (2.2)
- Dosage can be increased by 2 mg to 4 mg per dose every 1 to 4 days; maximum total daily dosage is 36 mg (2.2)
- Tizanidine pharmacokinetics differs between tablets and capsules, and when taken with or without food. These differences could result in a change in tolerability and control of symptoms. Consistent administration with respect to food is recommended. If substitution between dosage forms is necessary, take into consideration these pharmacokinetic differences. (2.2, 2.6, 12.3)
- Patients with renal impairment (creatinine clearance <25 mL/min) or hepatic impairment: use lower individual doses during titration. If higher doses are required, individual doses rather than dosing frequency should be increased. (2.3, 2.4)
- To discontinue Zanaflex, decrease dose slowly to minimize the risk of withdrawal adverse reactions (2.5)

3 DOSAGE FORMS AND STRENGTHS

- Capsules: 2 mg, 4 mg, or 6 mg (3)
- Tablets: 4 mg (3)

4 CONTRAINDICATIONS

- Concomitant use with strong CYP1A2 inhibitors (4, 7.1)
- Patients with a history of hypersensitivity to tizanidine or the ingredients in Zanaflex. (4, 5.5)

5 WARNINGS AND PRECAUTIONS

- Hypotension: monitor for signs and symptoms of hypotension, in particular in patients receiving concurrent antihypertensives; Zanaflex should not be used with other α2-adrenergic agonists (5.1, 7.7)
- Risk of liver injury: monitor ALTs; discontinue Zanaflex if liver injury occurs (5.2)
- Sedation: Zanaflex may interfere with everyday activities; sedative effects of Zanaflex, alcohol, and other central nervous system (CNS) depressants are additive (5.3, 7.4)
- Hallucinations: consider discontinuation of Zanaflex (5.4)

6 ADVERSE REACTIONS

The most common adverse reactions (greater than 10% of patients taking tizanidine and greater than in patients taking placebo) were dry mouth, somnolence, asthenia, and dizziness. (6.1)

To report SUSPECTED ADVERSE REACTIONS, contact Legacy Pharma Inc. at 1-8007277151 or FDA at 1-800-FDA-1088 or www.fda.gov/medwatch.

7 DRUG INTERACTIONS

Moderate or weak CYP1A2 inhibitors: avoid concomitant use; may cause hypotension, bradycardia, or excessive drowsiness; if concomitant use is necessary and adverse reactions occur, reduce Zanaflex dosage or discontinue. (7.2, 12.3)

8 USE IN SPECIFIC POPULATIONS

- Pregnancy: Based on animal data, may cause fetal harm (8.1)
- Geriatric use: Zanaflex should be used with caution in elderly patients because clearance is decreased four-fold (8.5)

FULL PRESCRIBING INFORMATION

1 INDICATIONS AND USAGE

Zanaflex is indicated for the treatment of spasticity in adults.

2 DOSAGE AND ADMINISTRATION

2.1 Recommended Evaluation and Testing Before and After Initiating Zanaflex

Monitoring of aminotransferase levels is recommended at baseline and 1 month after maximum dose is achieved [see Warnings and Precautions (5.2)] .

2.2 Recommended Dosage

The recommended starting dose is 2 mg by mouth every 6 to 8 hours, as needed, to a maximum of three doses in 24 hours.

Dosage can be gradually increased every 1 to 4 days by 2 mg to 4 mg at each dose based on clinical response and tolerability. The maximum total daily dosage is 36 mg. Single doses greater than 16 mg have not been studied.

There are pharmacokinetic differences when administering Zanaflex between the fed or fasted state [see Clinical Pharmacology (12.3)] . Zanaflex may be taken with or without food; however, consistent administration with respect to food is recommended to reduce variability in tizanidine plasma exposure.

Because of the short duration of therapeutic effect, treatment with Zanaflex should be reserved for those daily activities and times when relief of spasticity is most important.

2.3 Recommended Dosage in Patients with Renal Impairment

In patients with creatinine clearance < 25 mL/min, use lower individual doses during titration. If higher doses are required, the individual doses rather than dosing frequency should be increased [see Use in Specific Populations (8.6) and Clinical Pharmacology (12.3)] .

2.4 Recommended Dosage in Patients with Hepatic Impairment

In patients with hepatic impairment, use lower individual doses during titration. If higher doses are required, individual doses rather than dosing frequency should be increased [see Use in Specific Populations (8.7) and Clinical Pharmacology (12.3)] .

2.5 Discontinuation of Zanaflex

When discontinuing Zanaflex, particularly in patients who have been receiving high doses for long periods or who may be on concomitant treatment with narcotics, decrease the dosage by 2 mg to 4 mg per day to minimize the risk of withdrawal adverse reactions [see Drug Abuse and Dependence (9.3)] .

2.6 Switching Between With/Without Food and Different Tizanidine Dosage Forms

There are pharmacokinetic differences when:

1. switching between administration of Zanaflex with or without food
2. switching between dosage forms if being administered with food.

If these situations occur, monitor patients for therapeutic effect or adverse reactions [see Dosage and Administration (2.2) and Clinical Pharmacology (12.3)] .

3 DOSAGE FORMS AND STRENGTHS

Capsules

2 mg: Light blue opaque body with a light blue opaque cap with “2 MG” printed on the cap

4 mg: White opaque body with a blue opaque cap with “4 MG” printed on the cap

6 mg: Blue opaque body with a white stripe and blue opaque cap with “6 MG” printed on the cap

Tablets

4 mg white, uncoated tablets with a quadrisecting score on one side and debossed with “A594” on the other side

4 CONTRAINDICATIONS

Zanaflex is contraindicated in patients

- taking strong CYP1A2 inhibitors [see Drug Interactions (7.1)] .
- with a history of hypersensitivity to tizanidine or the ingredients in Zanaflex. Symptoms have included anaphylaxis and angioedema [see Warnings and Precautions (5.5)]

5 WARNINGS AND PRECAUTIONS

5.1 Hypotension

Zanaflex is an α2-adrenergic agonist that can produce hypotension [see Adverse Reactions (6.1) and Drug Interactions (7.5)] . Syncope has been reported in patients treated with tizanidine in the postmarketing setting. The risk of hypotension may be minimized by dose titration; monitoring for signs and symptoms of hypotension prior to dosage increase may minimize the risks associated with hypotension. In addition, patients moving from a supine to fixed upright position may be at increased risk for hypotension and orthostatic effects.

Monitor for hypotension when Zanaflex is used in patients receiving concurrent antihypertensive therapy. It is not recommended that Zanaflex be used with other α2-adrenergic agonists. Clinically significant hypotension (decreases in both systolic and diastolic pressure) has been reported with concomitant administration of tizanidine and strong CYP1A2 inhibitors [see Clinical Pharmacology (12.3)] . Therefore, concomitant use of Zanaflex with strong CYP1A2 inhibitors is contraindicated [see Contraindications (4) and Drug Interactions (7.1)] .

5.2 Liver Injury

Zanaflex may cause hepatocellular liver injury. Liver function test abnormality and hepatotoxicity have been observed with Zanaflex [see Adverse Reactions (6.1, 6.2)] . Monitoring of aminotransferase levels is recommended at baseline and 1 month after maximum dose is achieved, or if hepatic injury is suspected [see Dosage and Administration (2.1) and Use in Specific Populations (8.7)] .

5.3 Sedation

Zanaflex can cause sedation, which may interfere with everyday activity. In the multiple dose studies of Zanaflex, the prevalence of patients with sedation peaked following the first week of titration and then remained stable for the duration of the maintenance phase of the study [see Adverse Reactions (6.1)] . The CNS depressant effects of Zanaflex with alcohol and other CNS depressants (e.g., benzodiazepines, opioids, tricyclic antidepressants) may be additive [see Drug Interactions (7.4)] . Monitor patients who take Zanaflex with another CNS depressant for symptoms of excess sedation.

5.4 Hallucinosis/Psychotic-Like Symptoms

Zanaflex use has been associated with hallucinations. Formed, visual hallucinations or delusions were reported in 5 of 170 patients (3%) in two North American controlled clinical studies. Most of the patients were aware that the events were unreal. One patient developed psychosis in association with the hallucinations. One patient among these 5 continued to have problems for at least 2 weeks following discontinuation of tizanidine. Hallucinations have also been reported with tizanidine use in the postmarketing setting. Consider discontinuing Zanaflex in patients who develop hallucinations.

5.5 Hypersensitivity Reactions

Zanaflex can cause anaphylaxis. Signs and symptoms of hypersensitivity, including respiratory compromise, urticaria, and angioedema of the throat and tongue, have been reported. Zanaflex is contraindicated in patients with a history of hypersensitivity reactions to tizanidine [see Contraindications (4)] .

5.6 Withdrawal Adverse Reactions

Zanaflex can cause withdrawal adverse reactions, which include rebound hypertension, tachycardia, and hypertonia. To minimize the risk of these reactions, particularly in patients who have been receiving high doses of Zanaflex (20 to 28 mg daily) for long periods of time (9 weeks or more) or who may be on concomitant treatment with narcotics, the Zanaflex dosage should be decreased slowly [see Dosage and Administration (2.5)] .

6 ADVERSE REACTIONS

The following clinically significant adverse reactions are described elsewhere in other sections of the prescribing information:

- Hypotension [see Warnings and Precautions (5.1)]
- Liver Injury [see Warnings and Precautions (5.2)]
- Sedation [see Warnings and Precautions (5.3)]
- Hallucinosis/Psychotic-Like Symptoms [see Warnings and Precautions (5.4)]
- Hypersensitivity Reactions [see Warnings and Precautions (5.5)]
- Withdrawal Adverse Reactions [see Warnings and Precautions (5.6)]

6.1 Clinical Trials Experience

Because clinical studies are conducted under widely varying conditions, adverse reaction rates observed in the clinical studies of a drug cannot be directly compared to rates in the clinical studies of another drug and may not reflect the rates observed in clinical practice.

The safety of Zanaflex has been evaluated in three double-blind, randomized, placebo-controlled clinical studies [see Clinical Studies (14)] . Two studies were conducted in patients with multiple sclerosis and one in patients with spinal cord injury. Each study had a 13-week active treatment period which included a 3-week titration phase to the maximum tolerated dose up to 36 mg/day in three divided doses, a 9-week plateau phase where the dose of tizanidine was held constant and a 1-week dose tapering period. In all, 264 patients received tizanidine and 261 patients received placebo. Across the three studies approximately 51% of patients were women, and the median dose during the plateau phase ranged from 20 to 28 mg/day.

The most common adverse reactions (>10% of patients treated with Zanaflex) reported in multiple dose, placebo-controlled clinical studies involving 264 patients with spasticity were dry mouth, somnolence/sedation, asthenia (weakness, fatigue and/or tiredness), and dizziness. Three-quarters of the patients rated the reactions as mild to moderate and one-quarter of the patients rated the reactions as being severe. These adverse reactions appeared to be dose related.

Table 1lists adverse reactions that were reported in greater than 2% of patients in three multiple dose, placebo-controlled studies who received Zanaflex where the frequency in the Zanaflex group was greater than the placebo group.

Table 1: Multiple Dose, Placebo-Controlled Studies-Adverse Reactions Reported in >2% of Patients Treated with Zanaflex Tablets and Incidence Greater than Placebo
Adverse Reaction | Placebo N = 261 % | Zanaflex Tablet N = 264 %
Dry mouth | 10 | 49
Somnolence | 10 | 48
Asthenia [includes weakness, fatigue, and/or tiredness] | 16 | 41
Dizziness | 4 | 16
UTI | 7 | 10
Infection | 5 | 6
Liver test abnormality | 2 | 6
Constipation | 1 | 4
Vomiting | 0 | 3
Speech disorder | 0 | 3
Amblyopia (blurred vision) | <1 | 3
Urinary frequency | 2 | 3
Flu syndrome | 2 | 3
Dyskinesia | 0 | 3
Nervousness | <1 | 3
Pharyngitis | 1 | 3
Rhinitis | 2 | 3

In the single dose, placebo-controlled study involving 142 patients with spasticity due to multiple sclerosis (Study 1) [see Clinical Studies (14)] , the patients were specifically asked if they had experienced any of the four most common adverse reactions: dry mouth, somnolence (drowsiness), asthenia (weakness, fatigue and/or tiredness), and dizziness. In addition, hypotension and bradycardia were observed. The occurrence of these reactions is summarized in Table 2. Other events were, in general, reported at a rate of 2% or less.

Table 2: Single Dose, Placebo-Controlled Study-Common Adverse Reactions Reported
Adverse Reaction | Placebo N = 48 % | Zanaflex Tablet, 8mg, N = 45 % | Zanaflex Tablet, 16 mg, N = 49 %
Somnolence | 31 | 78 | 92
Dry mouth | 35 | 76 | 88
Asthenia [includes weakness, fatigue, and/or tiredness] | 40 | 67 | 78
Dizziness | 4 | 22 | 45
Hypotension | 0 | 16 | 33
Bradycardia | 0 | 2 | 10

6.2 Postmarketing Experience

The following adverse reactions have been identified during post approval use of Zanaflex. Because these reactions are reported voluntarily from a population of uncertain size, it is not always possible to reliably estimate their frequency or establish a causal relationship to drug exposure.

Cardiac Disorders: Ventricular tachycardia, decreased blood pressure

Hepatobiliary Disorders: Hepatotoxicity [see Warnings and Precautions (5.2)] , hepatitis

Musculoskeletal and Connective Tissue Disorders: arthralgia

Nervous System Disorders: Convulsion, paresthesia, tremor, muscle spasms

Psychiatric Disorders: Hallucinations [see Warnings and Precautions (5.4)] , depression

Skin and Subcutaneous Tissue Disorders: Stevens Johnson Syndrome, anaphylactic reaction [see Warnings and Precautions (5.5)] , exfoliative dermatitis, rash

7 DRUG INTERACTIONS

7.1 Strong CYP1A2 Inhibitors

Concomitant use of Zanaflex with strong cytochrome P450 1A2 (CYP1A2) inhibitors (e.g., fluvoxamine, ciprofloxacin) is contraindicated. Changes in pharmacokinetics of tizanidine when administered with a strong CYP1A2 inhibitor resulted in significantly decreased blood pressure, increased drowsiness, and increased psychomotor impairment [see Contraindications (4) and Clinical Pharmacology (12.3)] .

7.2 Moderate or Weak CYP1A2 Inhibitors

Concomitant use of Zanaflex with moderate or weak CYP1A2 inhibitors (e.g., zileuton, antiarrhythmics [amiodarone, mexiletine, propafenone, and verapamil], cimetidine, famotidine, oral contraceptives, acyclovir, and ticlopidine) should be avoided. If concomitant use is clinically necessary, and adverse reactions such as hypotension, bradycardia, or excessive drowsiness occur, reduce Zanaflex dosage or discontinue Zanaflex therapy [see Clinical Pharmacology (12.3)] .

7.3 Oral Contraceptives

Concomitant use of Zanaflex with oral contraceptives is not recommended. However, if concomitant use is clinically necessary and adverse reactions such as hypotension, bradycardia, or excessive drowsiness occur, reduce or discontinue Zanaflex therapy [see Clinical Pharmacology (12.3)] .

7.4 Alcohol and Other CNS Depressants

Alcohol increases the exposure of tizanidine after administration of Zanaflex. This was associated with an increase in adverse reactions of Zanaflex.

Concomitant use of Zanaflex with CNS depressants (e.g., alcohol, benzodiazepines, opioids, tricyclic antidepressants) may cause additive CNS depressant effects, including sedation. Monitor patients who take Zanaflex with another CNS depressant for symptoms of excess sedation [see Clinical Pharmacology (12.3)] .

7.5 α2-Adrenergic Agonists

Concomitant use of Zanaflex with other α2-adrenergic agonists is not recommended because hypotensive effects may be cumulative [see Warnings and Precautions (5.1)] .

7.6 Antihypertensive Medications

Concomitant use of Zanaflex with antihypertensive medications may cause additive hypotensive effects [see Warnings and Precautions (5.1)] . Monitor patients who take Zanaflex with antihypertensive medications for hypotension.

8 USE IN SPECIFIC POPULATIONS

8.1 Pregnancy

Risk Summary

There are no adequate data on the developmental risk associated with use of Zanaflex in pregnant women. In animal studies, administration of tizanidine during pregnancy resulted in developmental toxicity (embryofetal and postnatal offspring mortality and growth deficits) at doses less than those used clinically, which were not associated with maternal toxicity (see Animal Data).

In the U.S. general population, the estimated background risk of major birth defects and miscarriage in clinically recognized pregnancies is 2% - 4% and 15% - 20%, respectively. The background risk of major birth defects and miscarriage for the indicated population is unknown.

Data

Animal Data

Oral administration of tizanidine (0.3 to 100 mg/kg/day) to pregnant rats during the period of organogenesis resulted in embryofetal and postnatal offspring mortality and reductions in body weight at doses of 30 mg/kg/day and above. Maternal toxicity was observed at the highest dose tested. The no-effect dose for embryofetal developmental toxicity in rats (3 mg/kg/day) is similar to the maximum recommended human dose (MRHD) of 36 mg/day on a body surface area (mg/m^2) basis.

Oral administration of tizanidine (1 to 100 mg/kg/day) to pregnant rabbits during the period of organogenesis resulted in embryofetal and postnatal offspring mortality at all doses. Maternal toxicity was observed at the highest dose tested. Oral administration of tizanidine (10 and 30 mg/kg/day) during the perinatal period of pregnancy (2-6 days prior to delivery) resulted in increased postnatal offspring mortality at both doses. A no-effect dose for embryofetal developmental toxicity in rabbit was not identified. The lowest dose tested (1 mg/kg/day) is less than the MRHD on a mg/m^2basis.

In a pre- and postnatal development study in rats, oral administration of tizanidine (3 to 30 mg/kg/day) resulted in increased postnatal offspring mortality. A no-effect dose for pre- and postnatal developmental toxicity was not identified. The lowest dose tested (3 mg/kg/day) is similar to the MRHD on a mg/m^2basis, respectively.

8.2 Lactation

Risk Summary

There are no data on the presence of tizanidine in human milk, the effects on the breastfed infant, or the effects on human milk production. Animal studies have reported the presence of tizanidine in the milk of lactating animals.

The developmental and health benefits of breastfeeding should be considered along with the mother’s clinical need for Zanaflex and any potential adverse effects on the breastfed infant from Zanaflex or from the underlying maternal condition.

8.3 Females and Males of Reproductive Potential

There are no adequate and well-controlled studies in humans on the effect of Zanaflex on female or male reproductive potential. Oral administration of tizanidine to male and female rats resulted in adverse effects on fertility [see Nonclinical Toxicology (13.1)].

8.4 Pediatric Use

Safety and effectiveness in pediatric patients have not been established.

Juvenile Animal Toxicity Data

Oral administration of tizanidine (0, 1, 3, and 10 mg/kg/day) to juvenile rats from postnatal day (PND) 7 through PND 70 resulted in delayed sexual maturation in males at all doses, reduced body weight gain, delayed sexual maturation in females, and bilateral corneal crystals at the mid and high doses. Corneal crystals were still observed at the mid and high doses after a three-week recovery period. Neurobehavioral deficits were observed on a learning and memory task at the high dose. A no-effect dose for adverse effects on postnatal development not identified.

8.5 Geriatric Use

Zanaflex is known to be substantially excreted by the kidney, and the risk of adverse reactions to this drug may be greater in patients with impaired renal function. Because elderly patients are more likely to have decreased renal function, care should be taken in dose selection, and it may be useful to monitor renal function.

Clinical studies of Zanaflex did not include sufficient numbers of subjects aged 65 and over to determine whether they respond differently than younger subjects. Pharmacokinetic data showed that younger subjects cleared tizanidine faster than the elderly subjects [see Clinical Pharmacology (12.3)] . In elderly patients with renal insufficiency (creatinine clearance <25 mL/min), tizanidine clearance is reduced compared to healthy elderly subjects; this would be expected to lead to a longer duration of clinical effect. During titration, the individual doses should be reduced. If higher doses are required, individual doses rather than dosing frequency should be increased. Monitor elderly patients because they may have an increased risk for adverse reactions associated with Zanaflex.

8.6 Renal Impairment

In patients with renal insufficiency (creatinine clearance <25 mL/min), clearance of tizanidine was reduced [see Clinical Pharmacology (12.3)] . In these patients, dosage reduction is recommended [see Dosage and Administration (2.3)] .Because the risk of adverse reactions to Zanaflex may be greater in patients with impaired renal function, monitor these patients closely for the onset or increase in severity of common adverse reactions [see Adverse Reactions (6.1)]

8.7 Hepatic Impairment

Zanaflex should be used with caution in patients with hepatic impairment. The influence of hepatic impairment on the pharmacokinetics of tizanidine has not been evaluated. Because tizanidine is extensively metabolized in the liver, hepatic impairment would be expected to have significant effects on pharmacokinetics of tizanidine. [see Warnings and Precautions (5.2), and Clinical Pharmacology (12.3)] . In patients with hepatic impairment, dosage reduction is recommended [see Dosage and Administration (2.4)]

9 DRUG ABUSE AND DEPENDENCE

9.1 Controlled Substance

Zanaflex contains tizanidine, which is not a controlled substance.

9.2 Abuse

Abuse is the intentional, non-therapeutic use of a drug, even once, for its desirable psychological or physiological effects. Abuse potential was not evaluated in human studies. Rats were able to distinguish tizanidine from saline in a standard discrimination paradigm, after training, but failed to generalize the effects of morphine, cocaine, diazepam, or phenobarbital to tizanidine.

9.3 Dependence

Physical dependence is a state that develops as a result of physiological adaptation in response to repeated drug use, manifested by withdrawal signs and symptoms after abrupt discontinuation or a significant dose reduction of a drug. Tizanidine is closely related to clonidine, which is often abused in combination with narcotics and is known to cause symptoms of rebound upon abrupt withdrawal. Cases of rebound symptoms on sudden withdrawal of tizanidine have been reported. The case reports suggest that these patients were also misusing narcotics. Withdrawal symptoms included hypertension, tachycardia, hypertonia, tremor, and anxiety. Withdrawal symptoms are more likely to occur in cases where high doses are used, especially for prolonged periods, or with concomitant use of narcotics. If therapy needs to be discontinued, the dose should be decreased slowly to minimize the risk of withdrawal symptoms [see Dosage and Administration (2.5)] .

Monkeys were shown to self-administer tizanidine in a dose-dependent manner, and abrupt cessation of tizanidine produced transient signs of withdrawal at doses >35 times the maximum recommended human dose on a mg/m^2basis. These transient withdrawal signs (increased locomotion, body twitching, and aversive behavior toward the observer) were not reversed by naloxone administration.

10 OVERDOSAGE

A review of the safety surveillance database revealed cases of intentional and accidental Zanaflex overdose. Some of the cases resulted in fatality and many of the intentional overdoses were with multiple drugs, including CNS depressants. The clinical manifestations of tizanidine overdose were consistent with its known pharmacology. In the majority of cases, a decrease in sensorium was observed including lethargy, somnolence, confusion, and coma. Depressed cardiac function is also observed including most often bradycardia and hypotension. Respiratory depression is another common feature of tizanidine overdose.

Should overdose occur, ensure the adequacy of an airway and monitor cardiovascular and respiratory function. Dialysis is not likely to be an efficient method of removing tizanidine from the body [see Description (11)] . In general, symptoms resolve within one to three days following discontinuation of tizanidine and administration of appropriate therapy. Because of the similar mechanism of action, symptoms and management of tizanidine overdose are similar to that following clonidine overdose. For the most recent information concerning the management of overdose, contact a poison control center.

11 DESCRIPTION

Zanaflex®contains tizanidine hydrochloride as the active ingredient, which is a central alpha2-adrenergic agonist. Its chemical name is 5-chloro-4-(2-imidazolin-2-ylamino)-2,1,3-benzothiadiazole monohydrochloride. It has a molecular formula of C9H8ClN5S-HCl and a molecular weight of 290.2. Its structural formula is:

Tizanidine hydrochloride is a white to off-white, fine crystalline powder, which is odorless or with a faint characteristic odor. Tizanidine hydrochloride is slightly soluble in water and methanol; solubility in water decreases as the pH increases.

Zanaflex capsules are for oral administration and contain 2, 4, or 6 mg tizanidine (equivalent to 2.29 mg, 4.58 mg, and 6.87 mg tizanidine hydrochloride, respectively), and the inactive ingredients colorants, gelatin, hypromellose, silicon dioxide, sugar spheres, and titanium dioxide.

Zanaflex tablets are for oral administration and contain 4 mg tizanidine (equivalent to 4.58 mg tizanidine hydrochloride), and the inactive ingredients anhydrous lactose, colloidal silicon dioxide, microcrystalline cellulose, and stearic acid.

12 CLINICAL PHARMACOLOGY

12.1 Mechanism of Action

Tizanidine is a central alpha-2-adrenergic receptor agonist and presumably reduces spasticity by increasing presynaptic inhibition of motor neurons. The effects of tizanidine are greatest on polysynaptic pathways. The overall effect of these actions is thought to reduce facilitation of spinal motor neurons.

12.2 Pharmacodynamics

The CNS depressant effects of tizanidine and alcohol are additive [see Warnings and Precautions (5.3) and Drug Interactions (7.4)]

12.3 Pharmacokinetics

Tizanidine has linear pharmacokinetics over the doses studied in clinical development [1 mg (half the recommended dosage) to 20 mg].

Zanaflex capsules and tablets are bioequivalent to each other under fasting conditions, but not under fed conditions (see Absorption, Effect of Food).

Absorption

Following oral administration, tizanidine is essentially completely absorbed. The absolute oral bioavailability of tizanidine is approximately 40% (CV = 24%), due to extensive first-pass hepatic metabolism.

Effect of Food

There are pharmacokinetic differences between Zanaflex capsules and Zanaflex tablets with respect to administration with food.

A single dose of either two 4 mg tablets or two 4 mg capsules was administered under fed and fasting conditions in an open-label, four-period, randomized crossover study in 96 volunteers, of whom 81 were eligible for the statistical analysis. Pharmacokinetics under fed conditions were different than under fasting conditions and vary by dosage form.

Tablets or Capsules - Fasting

- Tmaxwas 1.0 hours after dosing
- T1/2was approximately 2 hours.

Tablets - Fed

- Mean Cmaxwas increased by approximately 30%
- Median Tmaxwas increased by 25 minutes, to 1 hour and 25 minutes.
- Extent of absorption was increased approximately 30%

Capsules - Fed

- Mean Cmaxwas decreased by 20% (consequently, approximately 66% the Cmax for the tablet when administered with food)
- Median Tmaxwas increased 2 to 3 hours
- Extent of absorption was increased approximately 10% (consequently, approximately 80% of the amount absorbed from the tablet administered with food)

Capsule Content Sprinkled on Applesauce

Compared to administration of an intact capsule while fasting:

- Cmaxand AUC was increased 15%–20%
- Tmaxwas decreased 15 minutes

Figure 1: Mean Tizanidine Concentration vs. Time Profiles For Zanaflex Tablets and Capsules (2 × 4 mg) Under Fasted and Fed Conditions

Distribution

Tizanidine is extensively distributed throughout the body with a mean steady state volume of distribution of 2.4 L/kg (CV = 21%) following intravenous administration in healthy adult volunteers. Tizanidine is approximately 30% bound to plasma proteins.

Elimination

Metabolism

Tizanidine has a half-life of approximately 2.5 hours (CV=33%). Approximately 95% of an administered dose is metabolized. The primary cytochrome P450 isoenzyme involved in tizanidine metabolism is CYP1A2. Tizanidine metabolites are not known to be active; their half-lives range from 20 to 40 hours.

Excretion

Following single and multiple oral dosing of^14C-tizanidine, an average of 60% and 20% of total radioactivity was recovered in the urine and feces, respectively.

Specific Populations

Geriatric Patients

No specific pharmacokinetic study was conducted to investigate age effects. Cross study comparison of pharmacokinetic data following single dose administration of 6 mg Zanaflex showed that younger subjects cleared the drug four times faster than the elderly subjects [see Use in Specific Populations (8.5)] .

Patients with Hepatic Impairment

The influence of hepatic impairment on the pharmacokinetics of tizanidine has not been evaluated. Because tizanidine is extensively metabolized in the liver, hepatic impairment would be expected to have significant effects on pharmacokinetics of tizanidine [see Use in Specific Populations (8.7)] .

Patients with Renal Impairment

Tizanidine clearance is reduced by more than 50% in elderly patients with renal insufficiency (creatinine clearance <25 mL/min) compared to healthy elderly subjects; this would be expected to lead to a longer duration of clinical effect [see Use in Specific Populations (8.6)] .

Gender Effects

No specific pharmacokinetic study was conducted to investigate gender effects. Retrospective analysis of pharmacokinetic data following single and multiple dose administration of 4 mg Zanaflex, however, showed that gender had no effect on the pharmacokinetics of tizanidine.

Drug Interactions

CYP1A2 Inhibitors

The effects of coadministration of fluvoxamine or ciprofloxacin, both strong CYP1A2 inhibitors, on the pharmacokinetics of a single 4 mg dose of Zanaflex was studied in 10 healthy subjects. The Cmax, AUC, and half-life of tizanidine increased by 12-fold, 33-fold, and 3-fold, respectively, with coadministration of fluvoxamine. The Cmaxand AUC of tizanidine increased by 7-fold and 10-fold, respectively, with coadministration of ciprofloxacin [see Contraindications (4)] .

There have been no clinical studies evaluating the effects of other CYP1A2 inhibitors on tizanidine [see Drug Interactions (7.2)] .

In vitro studies of cytochrome P450 isoenzymes using human liver microsomes indicate that neither tizanidine nor the major metabolites are likely to affect the metabolism of other drugs metabolized by cytochrome P450 isoenzymes.

Oral Contraceptives

No specific pharmacokinetic study was conducted to investigate interaction between oral contraceptives and Zanaflex. Retrospective analysis of population pharmacokinetic data following single and multiple dose administration of 4 mg Zanaflex, however, showed that women concurrently taking oral contraceptives had 50% lower clearance of tizanidine compared to women not on oral contraceptives [see Drug Interactions (7.3))] .

Acetaminophen

Tizanidine delayed the Tmaxof acetaminophen by 16 minutes. Acetaminophen did not affect the pharmacokinetics of tizanidine.

Alcohol

Alcohol increased the AUC and Cmaxof tizanidine by approximately 20% and 15%, respectively [see Drug Interactions (7.4)] .

13 NONCLINICAL TOXICOLOGY

13.1 Carcinogenesis, Mutagenesis, Impairment of Fertility

Carcinogenesis

Tizanidine was administered to mice for 78 weeks at oral doses up to 16 mg/kg/day, which is 2 times the maximum recommended human dose (MRHD) of 36 mg/day on a body surface area (mg/m^2) basis. Tizanidine was administered to rats for 104 weeks at oral doses up to 9 mg/kg/day, which is 2.5 times the MRHD on a mg/m^2basis. There was no increase in tumors in either species.

Mutagenesis

Tizanidine was negative in in vitro(bacterial reverse mutation [Ames], mammalian gene mutation, and chromosomal aberration test in mammalian cells) and in vivo(bone marrow micronucleus, and cytogenetics) assay.

Impairment of Fertility

Oral administration of tizanidine to rats prior to and during mating and continuing during early pregnancy in females resulted in reduced fertility in male and female rats at doses of 30 and 10 mg/kg/day, respectively. No effect on fertility was observed at doses of 10 (male) and 3 (female) mg/kg/day, which are approximately 3 times and similar to the MRHD, respectively, on a mg/m^2basis.

14 CLINICAL STUDIES

The efficacy of Zanaflex for the treatment of spasticity was demonstrated in two adequate and well-controlled studies in patients with multiple sclerosis or spinal cord injury (Studies 1 and 2).

Single-Dose Study in Patients with Multiple Sclerosis with Spasticity

In Study 1, 140 patients with spasticity caused by multiple sclerosis were randomized to receive single oral doses of 8 mg or 16 mg of Zanaflex, or placebo. Patients and assessors were blinded to treatment assignment and efforts were made to reduce the likelihood that assessors would become aware indirectly of treatment assignment (e.g., they did not provide direct care to patients and were prohibited from asking questions about side effects).

Response was assessed by physical examination; muscle tone was rated on a 5-point scale (Ashworth score) as follows:

- 0 = normal muscle tone
- 1 = slight spastic catch
- 2 = more marked muscle resistance
- 3 = considerable increase in tone, making passive movement difficult
- 4 = a muscle immobilized by spasticity

Spasm counts were also collected. Assessments were made at 1, 2, 3 and 6 hours after treatment. A statistically significant reduction of the Ashworth score for Zanaflex compared to placebo was detected at 1, 2, and 3 hours after treatment. Figure 2below shows a comparison of the mean change in muscle tone from baseline as measured by the Ashworth scale. The greatest reduction in muscle tone was 1 to 2 hours after treatment. By 6 hours after treatment, muscle tone in the 8 mg and 16 mg Zanaflex groups was indistinguishable from muscle tone in patients who received placebo. Within a given patient, improvement in muscle tone was correlated with plasma concentration. Plasma concentrations were variable from patient to patient at a given dose. Although 16 mg produced a larger effect, adverse reactions including hypotension were more common and more severe than in the 8 mg group. There were no differences in the number of spasms occurring in each group.

Figure 2: Single Dose Study—Mean Change in Muscle Tone from Baseline as Measured by the Ashworth Scale ± 95% Confidence Interval (A Negative Ashworth Score Signifies an Improvement in Muscle Tone from Baseline)

Seven-Week Study in Patients with Spinal Cord Injury with Spasticity

In a 7-week study (Study 2), 118 patients with spasticity secondary to spinal cord injury were randomized to either placebo or Zanaflex. Steps similar to those taken in the first study were employed to ensure the integrity of blinding.

Patients were titrated over 3 weeks up to a maximum tolerated dose or 36 mg daily given in three unequal doses (e.g., 10 mg given in the morning and afternoon and 16 mg given at night). Patients were then maintained on their maximally tolerated dose for 4 additional weeks (i.e., maintenance phase). Throughout the maintenance phase, muscle tone was assessed on the Ashworth scale within a period of 2.5 hours following either the morning or afternoon dose. The number of daytime spasms was recorded daily by patients.

At endpoint (the protocol-specified time of outcome assessment), there was a statistically significant reduction in muscle tone and frequency of spasms in the Zanaflex treated group compared to placebo. The reduction in muscle tone was not associated with a reduction in muscle strength (a desirable outcome), but also did not lead to any consistent advantage of Zanaflex treated patients on measures of activities of daily living. Figure 3below shows a comparison of the mean change in muscle tone from baseline as measured by the Ashworth scale.

Figure 3: Seven Week Study-Mean Change in Muscle Tone 0.5–2.5 Hours After Dosing as Measured by the Ashworth Scale ± 95% Confidence Interval (A Negative Ashworth Score Signifies an Improvement in Muscle Tone from Baseline)

16 HOW SUPPLIED/STORAGE AND HANDLING

16.1 How Supplied

Zanaflex Capsules

Zanaflex (tizanidine) capsules are two-piece hard gelatin shells containing 2 mg, 4 mg, or 6 mg tizanidine in bottles of 150 capsules available as follows.

- The 2 mg capsules have a light blue opaque body with a light blue opaque cap with “2 MG” printed on the cap: NDC 83107-001-15
- The 4 mg capsules have a white opaque body with a blue opaque cap with “4 MG” printed on the cap: NDC 83107-002-15
- The 6 mg capsules have a blue opaque body with a white stripe and blue opaque cap with “6 MG” printed on the capsules: NDC 83107-003-15

Zanaflex Tablets

Zanaflex (tizanidine) tablets are uncoated containing 4 mg tizanidine in bottles of 150 tablets. The tablets have a quadrisecting score on one side and are debossed with “A594” on the other side: NDC 83107-004-15.

16.2 Storage and Handling

Store at 20°C to 25°C (68°F to 77°F); excursions permitted between 15°C to 30°C (59°F to 86°F) [see USP Controlled Room Temperature].

Dispense in containers with child resistant closure.

17 PATIENT COUNSELING INFORMATION

Serious Drug Interactions

Advise patients they should not take Zanaflex if they are taking fluvoxamine or ciprofloxacin because of the increased risk of serious adverse reactions including severe lowering of blood pressure and sedation. Instruct patients to inform their healthcare providers when they start or stop taking any medication because of the risks associated with interaction between Zanaflex and other medicines [see Contraindications (4) and Drug Interactions (7)]. .

Zanaflex Dosing and Administration

Tell patients to take Zanaflex exactly as prescribed (consistently either with or without food) and not to switch between tablets and capsules [see Dosage and Administration (2)] . Inform patients that they should not take more Zanaflex than prescribed because of the risk of adverse events at single doses greater than 8 mg or total daily doses greater than 36 mg. Tell patients that they should not suddenly discontinue Zanaflex, because rebound hypertension and tachycardia may occur [see Warnings and Precautions (5.6)].

Hypotension

Warn patients that they may experience hypotension and to be careful when changing from a lying or sitting to a standing position [see Warnings and Precautions (5.1)] .

Sedation

Tell patients that Zanaflex may cause them to become sedated or somnolent and they should be careful when performing activities that require alertness, such as driving a vehicle or operating machinery [see Warnings and Precautions (5.3)] . Tell patients that the sedation may be additive when Zanaflex is taken in conjunction with drugs (baclofen, benzodiazepines) or substances (e.g., alcohol) that act as CNS depressants.

Remind patients that if they depend on their spasticity to sustain posture and balance in locomotion, or whenever spasticity is utilized to obtain increased function, that Zanaflex decreases spasticity and caution should be used.

Hypersensitivity Reactions

Inform patients of the signs and symptoms of severe allergic reactions and instruct them to discontinue Zanaflex and seek immediate medical care should these signs and symptoms occur [see Warnings and Precautions (5.5)] .

Zanaflex®capsules is a registered trademark of Legacy Pharma Inc. Zanaflex®tablets is a registered trademark of Legacy Pharma Inc.

Manufactured for:

Legacy Pharma Inc.

Georgetown, Grand Cayman

KY1-9012

PRINCIPAL DISPLAY PANEL

Zanaflex Capsules (tizanidine) 2 mg, NDC 83107-001-15 150s Bottle Label

PRINCIPAL DISPLAY PANEL

Zanaflex Capsules®(tizanidine) 4 mg - NDC 83107-002-15 - 150s Bottle Label

PRINCIPAL DISPLAY PANEL

Zanaflex Capsules®(tizanidine) 6 mg - NDC 83107-003-15 - 150s Bottle Label

PRINCIPAL DISPLAY PANEL

Zanaflex®(tizanidine) 4 mg Tablets - NDC 83107-004-15 - 150s Bottle Label